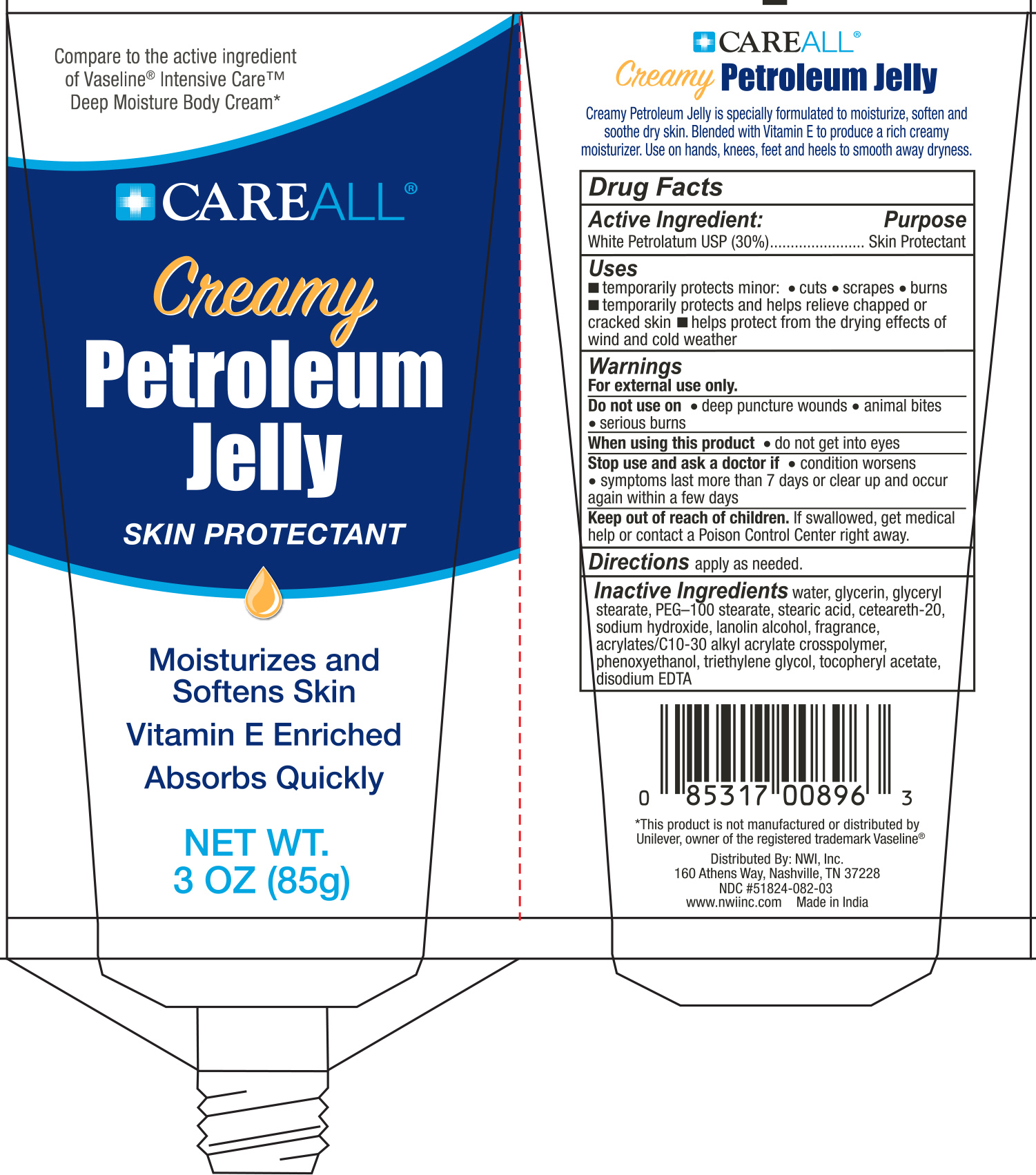 DRUG LABEL: CareALL Creamy Petroleum Jelly
NDC: 51824-082 | Form: CREAM
Manufacturer: New World Imports, Inc
Category: otc | Type: HUMAN OTC DRUG LABEL
Date: 20251201

ACTIVE INGREDIENTS: PETROLATUM 30 g/100 g
INACTIVE INGREDIENTS: WATER; GLYCERIN; GLYCERYL STEARATE; PEG-100 STEARATE; STEARIC ACID; POLYOXYL 20 CETOSTEARYL ETHER; SODIUM HYDROXIDE; LANOLIN ALCOHOLS; CARBOMER COPOLYMER TYPE A (ALLYL PENTAERYTHRITOL CROSSLINKED); PHENOXYETHANOL; TRIETHYLENE GLYCOL; .ALPHA.-TOCOPHEROL ACETATE; EDETATE DISODIUM

Active Ingredient

White Petrolatum USP

Purpose

Skin Protectant

Uses

- temporarily protects minor: cuts, scrapes and burns
- temporarily protects and helps relieve chapped or cracked skin
- helps protect from the drying effects of wind and cold weather

Warnings

For external use only.

Do not use on:

- deep puncture wounds
- animal bites
- serious burns.

When using this product, do not get into eyes.

Stop use and ask a doctor if:

•condition worsens

•symptoms last more than 7 days or clear up and occur again within a few days

Keep out of reach of children.If swallowed, get medical help or contact a Poison Control Center right away.

Directions

apply as needed.

Inactive Ingredients

water, glycerin, glyceryl stearate, PEG—100 stearate, stearic acid, ceteareth-20, sodium hydroxide, lanolin alcohol, fragrance, acrylates/C10-30 alkyl acrylate crosspolymer, phenoxyethanol, triethylene glycol, tocopheryl acetate, disodium EDTA